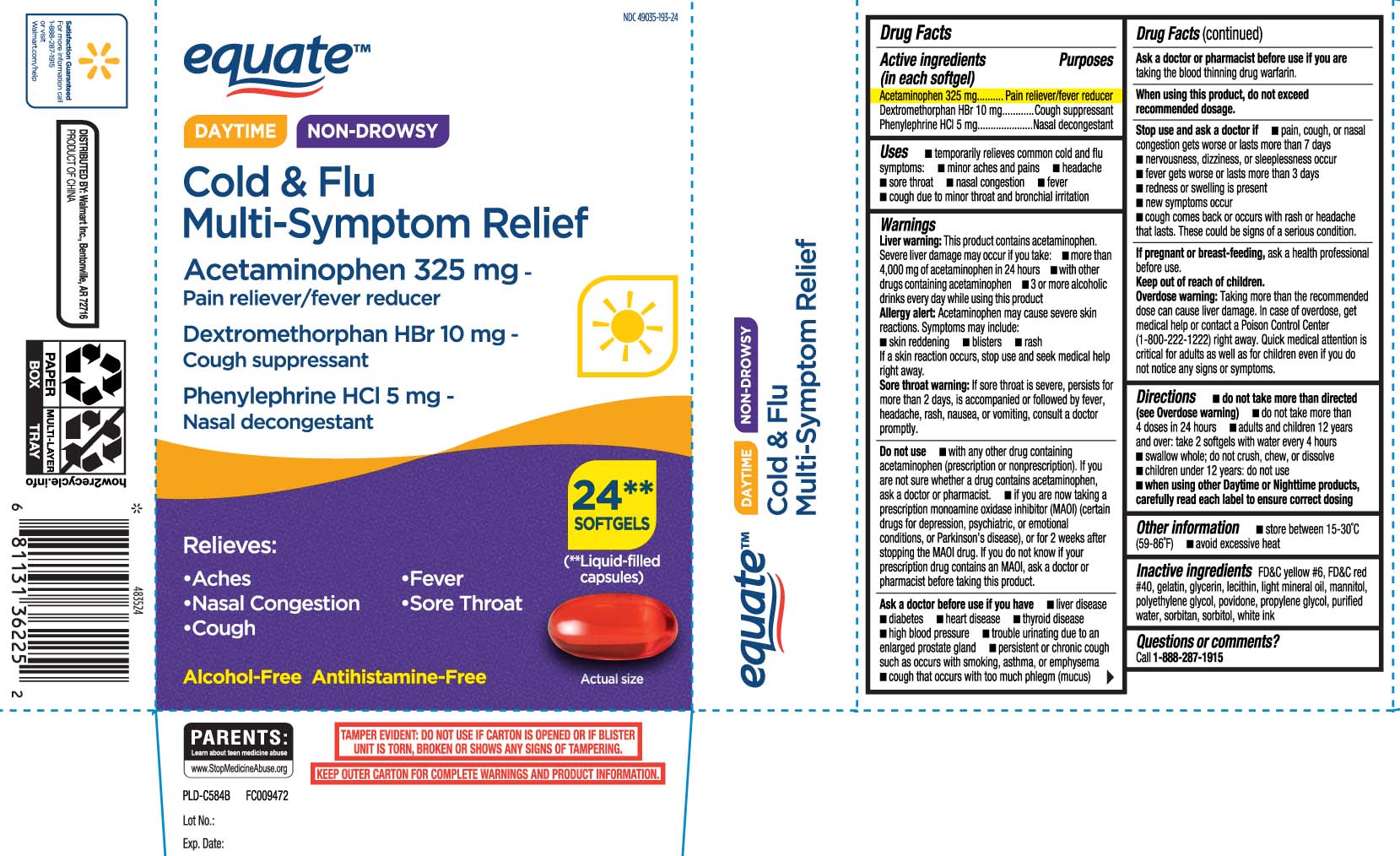 DRUG LABEL: Cold and Flu
NDC: 49035-193 | Form: CAPSULE, LIQUID FILLED
Manufacturer: EQUATE (Wal-Mart Stores, Inc.) (see also WAL-MART INC)
Category: otc | Type: HUMAN OTC DRUG LABEL
Date: 20250619

ACTIVE INGREDIENTS: ACETAMINOPHEN 325 mg/1 1; DEXTROMETHORPHAN HYDROBROMIDE 10 mg/1 1; PHENYLEPHRINE HYDROCHLORIDE 5 mg/1 1
INACTIVE INGREDIENTS: FD&C YELLOW NO. 6; GLYCERIN; PROPYLENE GLYCOL; WATER; LECITHIN, SOYBEAN; FD&C RED NO. 40; GELATIN; POLYETHYLENE GLYCOL, UNSPECIFIED; SORBITOL; POVIDONE; SORBITAN; LIGHT MINERAL OIL; MANNITOL

Drug Facts

Active ingredients (in each softgel)

Acetaminophen 325 mg

Dextromethoprhan HBr 10 mg

Phenlyephrine HCl 5 mg

Purposes

Pain reliever/fever reducer

Cough suppressant

Nasal decongestant

Uses

- temporarily relieves these common cold/flu symptoms:
  - minor aches and pains
  - headache
  - sore throat
  - fever
  - nasal congestion
  - cough due to minor throat and bronchial irritation

Warnings

Liver warning: This product contains acetaminophen. Severe liver damage may occur if you take:

- more than 4,000 mg of acetaminophen I 24 hours
- with other drugs containing acetaminophen
- 3 or more alcoholic drinks everyday while using this product

Allery alert: Acetaminophen may cause severe skin reactions. Symptoms may include:

- skin reddening
- blisters
- rash

If a skin reaction occurs, stop use and seek medical help right away

Sore throat warning: If sore throat is severe, persists for more than 2 days, is accompanied or followed by fever, headache, rash, nausea, or vomiting, consult a doctor promptly.

Do not use

- if you are now taking a prescription monoamine oxidase inhibitor (MAOI) (certain drugs for depression, psychiatric, or emotional conditions, or Parkinson's disease) or for 2 weeks after stopping the MAOI drug. If you do not know if your prescription drug contains an MAOI, ask a doctor or pharmacist before taking this product.
- with any other drug containing acetaminophen (prescription or non-prescription). If you are not sure whether a drug contains acetaminophen, ask a doctor or pharmacist.

Ask a doctor before use if the user has

- liver disease
- diabetes
- heart disease
- thyroid disease
- high blood pressure
- persistent or chronic cough such as occurs with smoking, asthma or emphysema
- cough that occurs with too much phlegm (mucus)
- trouble urinating due to an enlarged prostate gland

Ask a doctor or pharmacist before use if you are

taking the blood thinning drug warfarin.

When using this product,

do not exceed recommended dosage.

Stop use and ask a doctor if

- pain, cough or nasal congestion gets worse or lasts more than 7 days
- nervousness, dizziness, or sleeplessness occur
- fever gets worse or lasts more than 3 days
- redness or swelling is present
- new symptoms occur
- cough comes back or occurs, with rash or headache that lasts.

These could be signs of a serious condition.

If pregnant or breast-feeding,

ask a health professional before use.

Keep out of reach of children.

Overdose warning: Taking more than the recommended dose (overdose) may cause liver damage. In case of overdose, get medical help or contact a Poison Control Center (1-800-222-1222) right away. Quick medical attention is critical for adults as well as for children even if you do not notice any signs or symptoms.

Directions

- do not take more than directed (see overdose warning)
- do not take more than 4 doses in 24-hour period
- adults and children 12 years and over: take 2 softgels with water every 4 hours
- swallow whole; do not crush, chew, or dissolve
- children under 12 years: do not use
- When using Day Time and Night Time products, carefully read each label to ensure correct dosing

Other information

- store between 15-30ºC (59-86º)
- avoid excessive heat

Inactive ingredients

FD&C yellow #6, FD&C red #40, gelatin, glycerin, lecithin, light mineral oil, mannitol, polyethylene glycol, povidone, propylene glycol, purified water, sorbitan, sorbitol white ink

Questions or comments?

Call 1-888-287-1915

Principal Display Panel

DAYTIME NON-DROWSY

Cold & Flu

Multi-Symptom Relief

Acetaminophen 325 mg

Pain reliever/fever reducer

Dextromethorphan HBr 10 mg

Cough suppressant

Phenylephrine HCl 5 mg

Nasal decongestant

Relieves:

- Aches
- fever
- Nasal Congestion
- Sore throat
- Cough

Alcohol-Free

Antihistamine-Free

SOFTGELS**

(**Liquid-filled capsules)

TAMPER EVIDENT: DO NOT USE IF CARTON IS OPENED OR IF BLISTER UNIT IS TORN, BROKEN OR SHOW ANY SIGNS OR TAMPERING.

KEEP OUTER CARTON FOR COMPLETE WARNINGS AND PRODUCT INFORMATION.

DISTRIBUTED BY:

Walmart Inc.,

Bentonville, AR 72716

Package Label

EQUATE Daytime Non-Drowsy Cold & Flu Relief